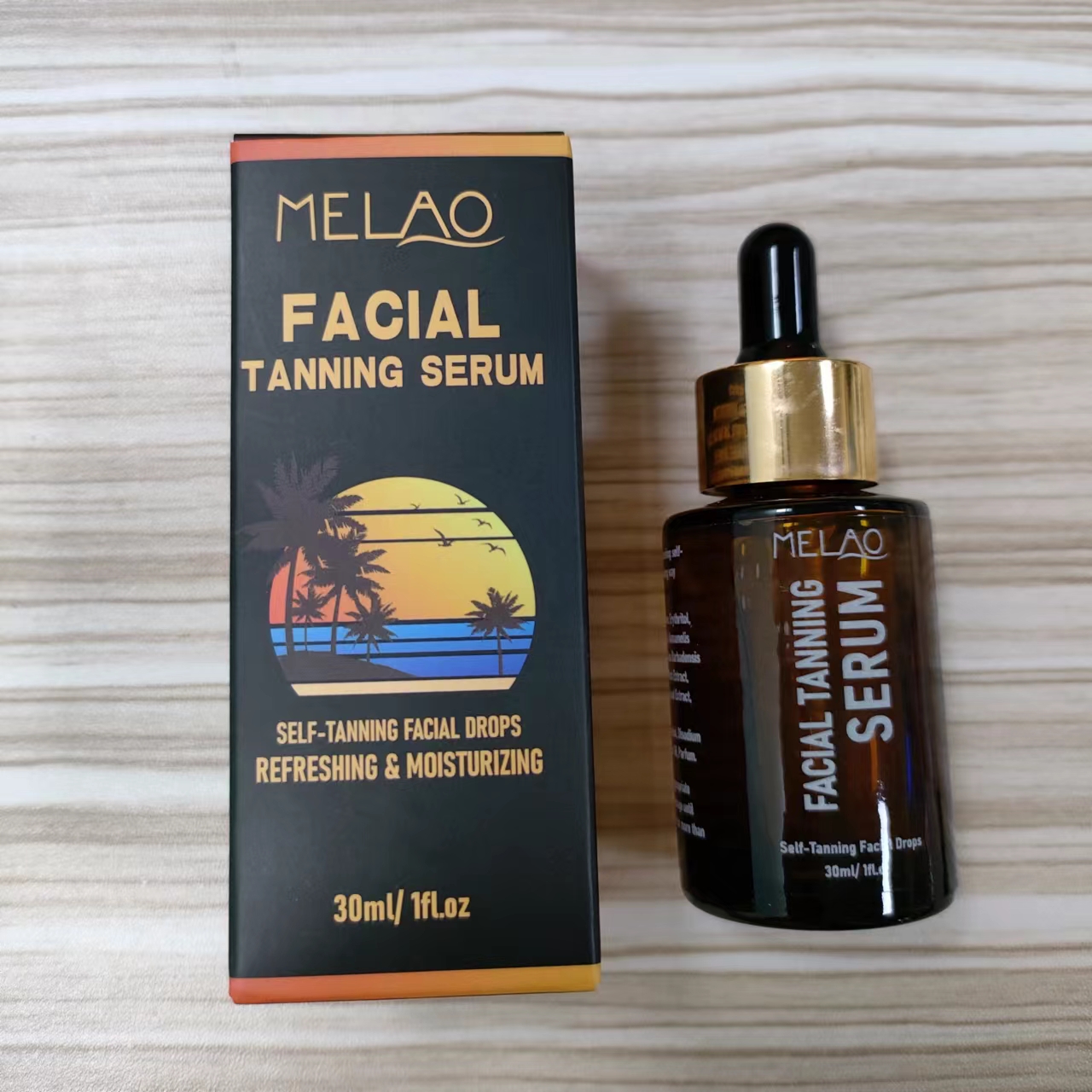 DRUG LABEL: MELAO FACIAL TANNING SERUM
NDC: 74458-551 | Form: OIL
Manufacturer: Guangzhou Yilong Cosmetics Co., Ltd
Category: otc | Type: HUMAN OTC DRUG LABEL
Date: 20241028

ACTIVE INGREDIENTS: DIHYDROXYACETONE 10 g/100 mL
INACTIVE INGREDIENTS: TARAXACUM OFFICINALE (DANDELION) ROOT; SAURURUS CHINENSIS WHOLE; XANTHAN GUM; HAMAMELIS VIRGINIANA (WITCH HAZEL) LEAF EXTRACT; PARFUMIDINE; HYDROXYACETOPHENONE; WATER; SODIUM HYALURONATE; ERYTHRITOL; STEPHANIA TETRANDRA ROOT; PEG-40 HYDROGENATED CASTOR OIL; 1,2-HEXANEDIOL; EDETATE DISODIUM; ALOE BARBADENSIS LEAF EXTRACT

MELAO FACIAL TANNING SERUM

ACTIVE INGREDIENT

Dihydroxyacetone

INACTIVE INGREDIENT

Water

Erythritol

Xanthan Gum

Sodium Hyaluronate

Hamamelis Virginiana (Witch Hazel) Extract

Saururus Chinensis Leaf/Root Extract

Aloe Barbadensis Extract

Taraxacum Officinale (Dandelion) Leaf

Extract

Stephania Tetrandra Root Extract

Hydroxyacetophenone

1,2-Hexanediol

Disodium EDTA

PEG-40 Hydrogenated Castor Oil

Parfum

PURPOSE

Self-tanning.

DOSAGE AND ADMINISTRATION

Apply an appropriate amount evenly on the skin and massage until absorbed. Can be used with cream for more than four hours forbetter results.

INDICATIONS AND USAGE

Apply an appropriate amount evenly on the skin and massage until absorbed. Can be used with cream for more than four hours forbetter results.

WARNINGS

For external use only.

Stop use and ask a doctor if rash occurs.

Do not use on damaged or broken skin.

When using this product keep out of eyes. Rinse with water to remove.

Keep out of reach of children. If swallowed, get medical help or contact a Poison Control Center right away.